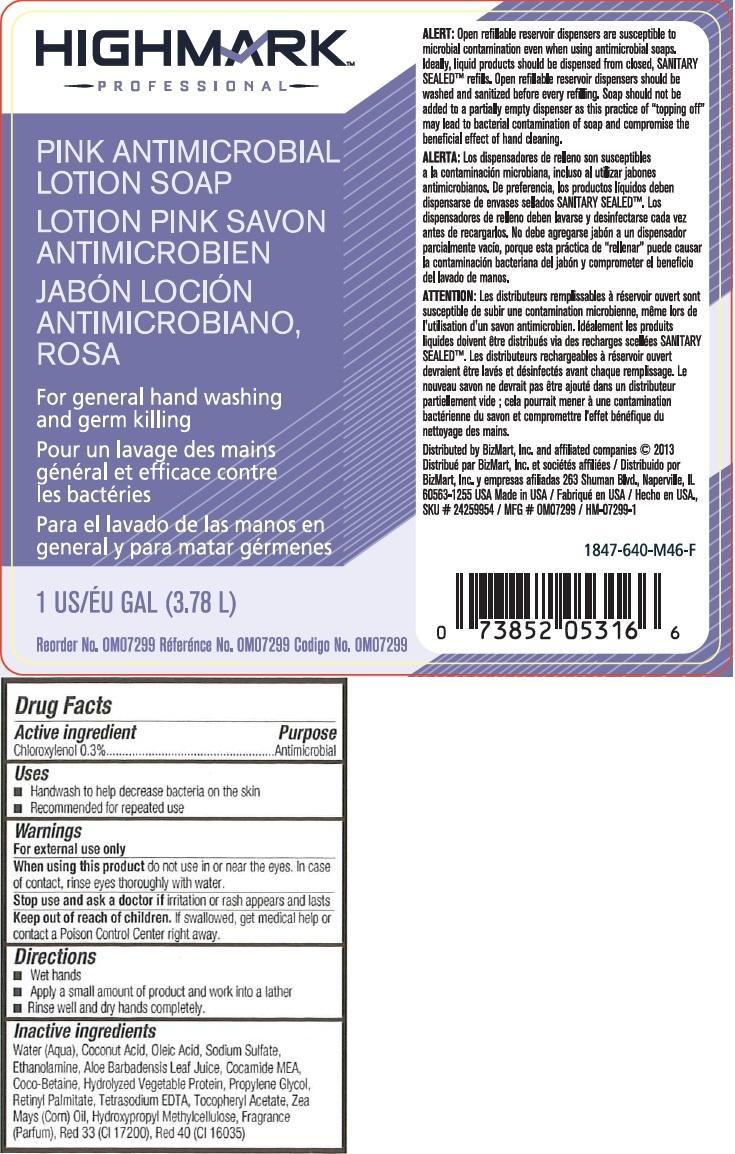 DRUG LABEL: HighMark Professional Pink Antimicrobial Ltn Sp
NDC: 61139-422 | Form: LIQUID
Manufacturer: Office Max, Inc.
Category: otc | Type: HUMAN OTC DRUG LABEL
Date: 20131122

ACTIVE INGREDIENTS: CHLOROXYLENOL 0.003 mg/1 mL
INACTIVE INGREDIENTS: WATER; COCONUT ACID; OLEIC ACID; SODIUM SULFATE; MONOETHANOLAMINE; ALOE VERA LEAF; COCO MONOETHANOLAMIDE; COCO-BETAINE; PROPYLENE GLYCOL; VITAMIN A PALMITATE; EDETATE SODIUM ; .ALPHA.-TOCOPHEROL ACETATE; CORN OIL; HYPROMELLOSES; D&C RED NO. 33; FD&C RED NO. 40

High Mark Professional Pink Antimicrobial Lotion Soap

Active ingredient

Chloroxylenol 0.3%

Purpose

Antimicrobial

Use

Handwash to help decrease bacteria on the skin

Recommended for repeated use

Directions

Wet hands

Apply a small amount of product and work into a lather

Rinse well and dry hands completely

Inactive ingredients

Water (Aqua), Coconut Acid, Oleic Acid, Sodium Sulfate, Ethanolamine, Aloe Barbadensis Leaf Juice, Cocamide MEA, Coco-Betaine, Hydrolyzed Vegetable Protein, Propylene Glycol, Retinyl Palmitate, Tetrasodium EDTA, Tocopheryl Acetate, Zea Mays (Corn) Oil, Hydroxypropyl Methylcellulose, Fragrance (Parfum), Red 33 (CI 17200), Red 40 (CI 16035)

Warnings

For external use only

When using this product do not use in or near the eyes. In case of contact, rinse eyes thoroughly with water.

Stop use and ask a doctor if irritation or rash appears and lasts.

Keep out of reach of children. If swallowed, get medical help or contact a Poison Control Center right away.

PACKAGE LABEL

For general hand washing and germ killing.

Alert Open refillable reservoir dispensers are susceptible to microbial contamination even when using antimicrobial soaps. Ideally, liquid products should be dispensed from closed, SANITARY SEALEDTM refills. Open refillable reservoir dispensers should be washed and sanitized before every refilling. Soaps should not be added to a partially empty dispenser as this practice of "topping off" may lead to bacterial contamination of soaps and compromise the beneficial effects of hand cleaning.